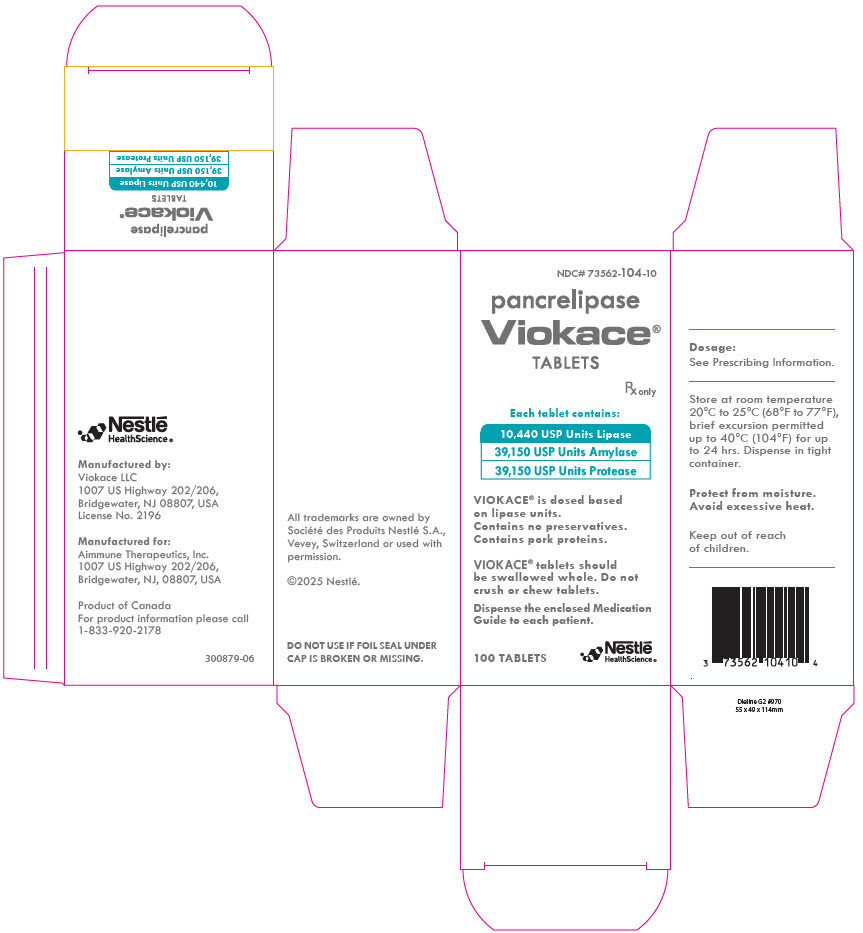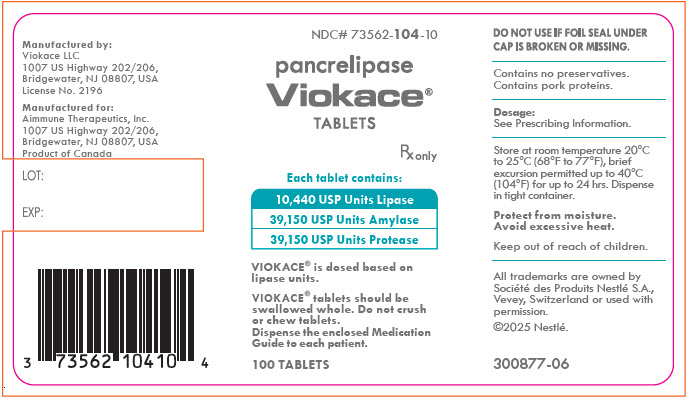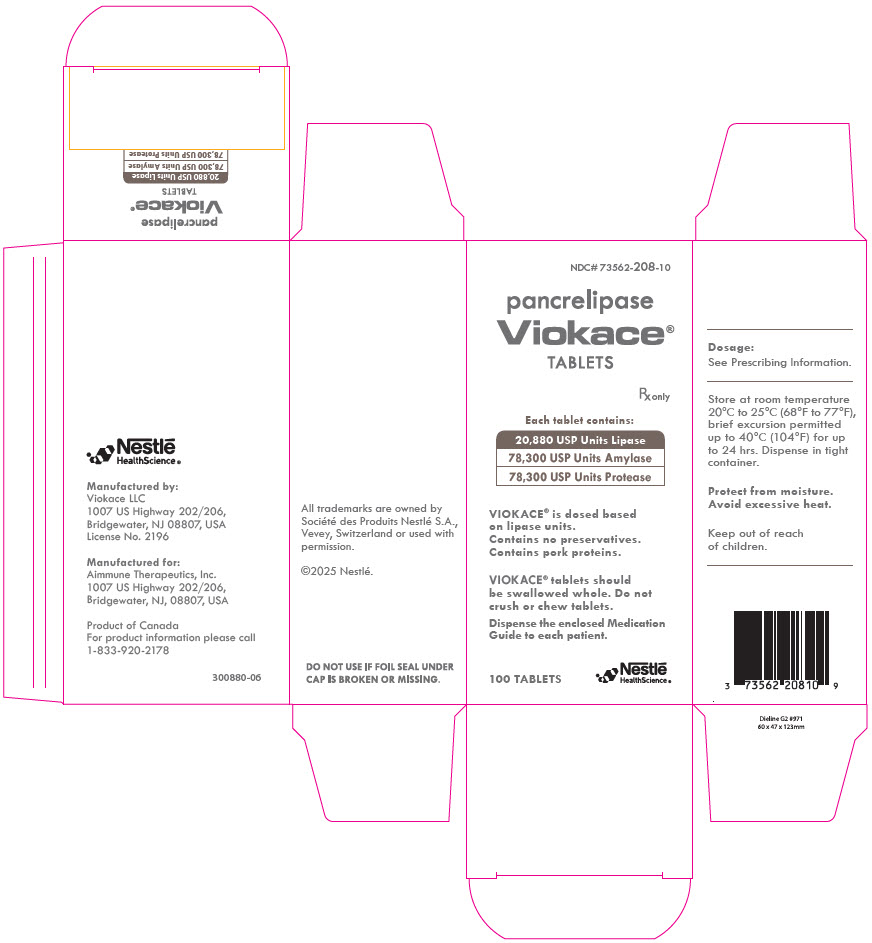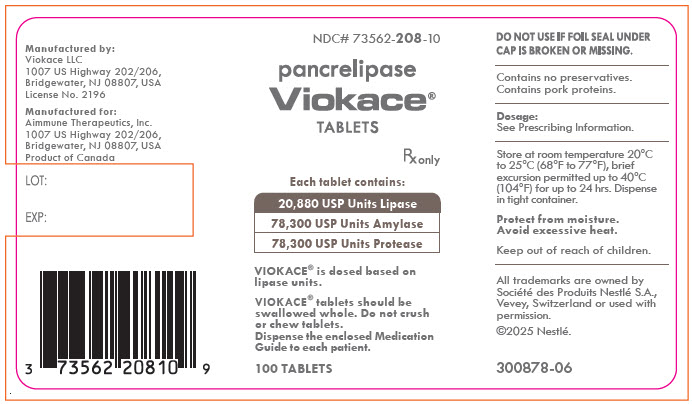 DRUG LABEL: Viokace
NDC: 73562-104 | Form: TABLET
Manufacturer: Aimmune Therapeutics, Inc.
Category: prescription | Type: HUMAN PRESCRIPTION DRUG LABEL
Date: 20250814

ACTIVE INGREDIENTS: PANCRELIPASE LIPASE 10440 [USP'U]/1 1; PANCRELIPASE PROTEASE 39150 [USP'U]/1 1; PANCRELIPASE AMYLASE 39150 [USP'U]/1 1
INACTIVE INGREDIENTS: LACTOSE MONOHYDRATE; CROSCARMELLOSE SODIUM; STEARIC ACID; MICROCRYSTALLINE CELLULOSE; SILICON DIOXIDE; TALC

HIGHLIGHTS OF PRESCRIBING INFORMATION

These highlights do not include all the information needed to use VIOKACE safely and effectively. See full prescribing information for VIOKACE
VIOKACE®(pancrelipase) tablets, for oral use
Initial U.S. Approval: 2012

1. INDICATIONS AND USAGE

VIOKACE, in combination with a proton pump inhibitor, is indicated for the treatment of exocrine pancreatic insufficiency due to chronic pancreatitis or pancreatectomy in adults. (1)

2. DOSAGE AND ADMINISTRATION

Important Dosing Information (2.1)

- VIOKACE is a mixture of enzymes including lipases, proteases, and amylases and dosing is based on lipase units. Dosing scheme based on actual body weight or fat ingestion.
- Individualize the dosage based on clinical symptoms, the degree of steatorrhea present, and the fat content of the diet.
- Do not exceed 2,500 lipase units/kg/meal, 10,000 lipase units/kg/day, or 4,000 lipase units/g fat ingested/day without further investigation. (5.1)
- The total daily dosage should reflect approximately three meals plus two or three snacks per day. With each snack, administer approximately half the prescribed dose for a meal.
- Do not substitute other pancreatic enzyme products for VIOKACE. When switching from another pancreatic enzyme product to VIOKACE, monitor patients for clinical symptoms of exocrine pancreatic insufficiency and titrate the dosage as needed.

Recommended Dosage

- Adult Patients: The recommended initial starting dosage is 500 lipase units/kg/meal.
- Titrate the dosage to 2,500 lipase units/kg/meal, 10,000 lipase units/kg/day, or 4,000 lipase units/g fat ingested/day. Higher dosages may be administered if documented effective by fecal fat measures or improvement in malabsorption.

Preparation and Administration Instructions

- Swallow tablets whole; do not crush or chew VIOKACE tablets. (2.3)
- Consume sufficient liquids to ensure complete swallowing of VIOKACE tablets. (2.3, 5.2)

3. DOSAGE FORMS AND STRENGTHS

Tablets (3):

- 10,440 USP units of lipase; 39,150 USP units of protease; and 39,150 USP units of amylase
- 20,880 USP units of lipase; 78,300 USP units of protease; and 78,300 USP units of amylase

4. CONTRAINDICATIONS

None. (4)

5. WARNINGS AND PRECAUTIONS

- Fibrosing Colonopathy: Associated with high doses, usually over prolonged use and in pediatric patients with cystic fibrosis. Colonic stricture reported in pediatric patients less than 12 years of age with dosages exceeding 6,000 lipase units/kg/meal. Monitor during treatment for progression of preexisting disease. Do not exceed the recommended dosage, unless clinically indicated. (2.1, 5.1)
- Irritation of the Oral Mucosa: May occur if tablets are crushed or chewed. (5.2)
- Hyperuricemia: Reported with high dosages, consider monitoring blood uric acid levels in patients with gout, renal impairment, or hyperuricemia. (5.3)
- Risk of Viral Transmission: The presence of porcine viruses that might infect humans cannot be definitely excluded. (5.4)
- Hypersensitivity Reactions: Monitor patients with known reactions to proteins of porcine origin. If symptoms occur, initiate appropriate medical management; consider the risks and benefits of continued treatment. (5.5)
- Potential for Exacerbation of Symptoms of Lactose Intolerance: tablets contain lactose monohydrate. Patients who have lactose intolerance may not be able to tolerate VIOKACE. (5.6)

6. ADVERSE REACTIONS

Most common adverse reactions (≥7%) are: anal pruritus and biliary tract stones. (6.1)

To report SUSPECTED ADVERSE REACTIONS, contact Aimmune Therapeutics, Inc at 1-833-AIM2KNO (1-833-246-2566) or FDA at 1-800-FDA-1088 or www.fda.gov/medwatch.

8. USE IN SPECIFIC POPULATIONS

- Pediatrics: VIOKACE use in pediatric patients may result in suboptimal weight gain, malnutrition and/or need for larger doses. The safety and effectiveness of VIOKACE in pediatric patients have not been established. (8.4)

FULL PRESCRIBING INFORMATION

1. INDICATIONS AND USAGE

VIOKACE, in combination with a proton pump inhibitor, is indicated for the treatment of exocrine pancreatic insufficiency due to chronic pancreatitis or pancreatectomy in adults.

2. DOSAGE AND ADMINISTRATION

2.1. Important Dosing Information

VIOKACE is a mixture of enzymes including lipases, proteases, and amylases. VIOKACE dosing is based on lipase units.

- Administer VIOKACE with a proton pump inhibitor.
- Use either an actual body weight or fat ingestion-based dosing scheme.
- Start at the lowest recommended dosage and individualize the dosage based on clinical symptoms, the degree of steatorrhea present, and the fat content of the diet. Changes in dosage may require an adjustment period of several days.
- Do not exceed 2,500 lipase units/kg/meal, 10,000 lipase units/kg/day, or 4,000 lipase units/g fat ingested/day without further investigation [see Warnings and Precautions (5.1)]. Higher dosages may be administered if they are documented to be effective by fecal fat measures or an improvement in signs or symptoms of malabsorption including measures of nutritional status.
- The total daily dosage should reflect approximately three meals plus two or three snacks per day. With each snack, administer approximately half the prescribed VIOKACE dose for a meal.
- Do not substitute other pancreatic enzyme products for VIOKACE. When switching from another pancreatic enzyme product to VIOKACE, monitor patients for clinical symptoms of exocrine pancreatic insufficiency and titrate the dosage as needed.

2.2. Recommended Dosage

Adult Patients:

The recommended oral initial starting dosage of VIOKACE is 500 lipase units/kg/meal.

If signs and symptoms of malabsorption persist, increase the dosage. Titrate to a maximum of either 2,500 lipase units/kg/meal, 10,000 lipase units/kg/day, or 4,000 lipase units/grams of fat ingested/day.

2.3. Preparation and Administration Instructions

Adult Patients:

- Take VIOKACE with meals or snacks. If a dose is missed, take the next dose with the next meal or snack.
- Swallow tablets whole. Do not crush or chew VIOKACE tablets.
- Consume sufficient liquids (water) to ensure complete swallowing of VIOKACE tablets [see Warnings and Precautions (5.2)].

3. DOSAGE FORMS AND STRENGTHS

Tablets are available in the following strengths:

- 10,440 USP units of lipase; 39,150 USP units of protease; and 39,150 USP units of amylase as a tan, round, biconvex tablet with VIO9111 engraved on one side and 9111 on the other side.
- 20,880 USP units of lipase; 78,300 USP units of protease; and 78,300 USP units of amylase as a tan, oval, biconvex tablet with V^16 engraved on one side and 9116 on the other side.

4. CONTRAINDICATIONS

None.

5. WARNINGS AND PRECAUTIONS

5.1. Fibrosing Colonopathy

Fibrosing colonopathy has been reported following treatment with pancreatic enzyme products. Fibrosing colonopathy is a rare, serious adverse reaction initially described in association with use of high-dose pancreatic enzyme products, usually over a prolonged period of time and most commonly reported in pediatric patients with cystic fibrosis. Pancreatic enzyme products exceeding 6,000 lipase units/kg/meal have been associated with colonic stricture, a complication of fibrosing colonopathy, in pediatric patients less than 12 years of age. The underlying mechanism of fibrosing colonopathy remains unknown.

If there is a history of fibrosing colonopathy, monitor patients during treatment with VIOKACE because some patients may be at risk of progressing to colonic stricture formation. It is uncertain whether regression of fibrosing colonopathy occurs. Do not exceed the recommended dosage of either 2,500 lipase units/kg/meal, 10,000 lipase units/kg/day, or 4,000 lipase units/g fat ingested/day without further investigation. Higher dosages may be administered if they are documented to be effective by fecal fat measures or an improvement in signs or symptoms of malabsorption including measures of nutritional status. Patients receiving dosages higher than 6,000 lipase units/kg/meal should frequently monitored for symptoms of fibrosing colonopathy and the dosage decreased or titrated downward to a lower range if clinically appropriate [see Dosage and Administration (2.1)].

5.2. Irritation of the Oral Mucosa

Crushing or chewing VIOKACE tablets can result in irritation of the oral mucosa, and/or loss of enzyme activity. Instruct the patient to swallow tablets whole. Do not crush or chew VIOKACE tablets. Consume sufficient liquids immediately following administration of VIOKACE to ensure complete swallowing [see Dosage and Administration (2.3)].

5.3. Hyperuricemia

Pancreatic enzyme products contain purines that may increase blood uric acid levels. High dosages have been associated with hyperuricosuria and hyperuricemia [see Overdosage (10)].

Consider monitoring blood uric acid levels in patients with gout, renal impairment, or hyperuricemia during treatment with VIOKACE.

5.4. Risk of Viral Transmission

VIOKACE is sourced from pancreatic tissue from pigs used for food consumption. Although the risk that VIOKACE will transmit an infectious agent to humans has been reduced by testing for certain viruses during manufacturing and by inactivating certain viruses during manufacturing, there is a theoretical risk for transmission of viral disease, including diseases caused by novel or unidentified viruses. Thus, the presence of porcine viruses that might infect humans cannot be definitely excluded. However, no cases of transmission of an infectious illness associated with the use of porcine pancreatic extracts have been reported.

5.5. Hypersensitivity Reactions

Severe hypersensitivity reactions including anaphylaxis, asthma, hives, and pruritus have been reported with pancreatic enzyme products [see Adverse Reactions (6.2)]. If symptoms occur, initiate appropriate medical management.

Monitor patients with a known hypersensitivity reaction to proteins of porcine origin for hypersensitivity reactions during treatment with VIOKACE. The risks and benefits of continued VIOKACE treatment in patients with severe hypersensitivity reactions should be taken into consideration with the overall clinical needs of the patient.

5.6. Potential for Exacerbation of Symptoms of Lactose Intolerance

VIOKACE tablets contain lactose monohydrate [see Description (11)]. Patients who have lactose intolerance may not be able to tolerate VIOKACE.

6. ADVERSE REACTIONS

The following serious or otherwise important adverse reactions are described elsewhere in the labeling:

- Fibrosing Colonopathy [see Warnings and Precautions (5.1)]
- Irritation of the Oral Mucosa [see Warnings and Precautions (5.2)]
- Hyperuricemia [see Warnings and Precautions (5.3)]
- Risk of Viral Transmission [see Warnings and Precautions (5.4)]
- Hypersensitivity Reactions [see Warnings and Precautions (5.5)]
- Potential for Exacerbation of Symptoms of Lactose Intolerance [see Warnings and Precautions (5.6)]

6.1. Clinical Trials Experience

Because clinical trials are conducted under widely varying conditions, adverse reaction rates observed in the clinical trials of a drug cannot be directly compared to the rates in the clinical trials of another drug and may not reflect the rates observed in practice.

The data described below reflect exposure to VIOKACE in 30 adult patients with exocrine pancreatic insufficiency due to chronic pancreatitis or pancreatectomy in a single, multicenter, randomized, parallel, placebo-controlled, double-blind study [see Clinical Studies (14)].

Adverse reactions that were reported in at least 2 VIOKACE-treated patients (greater than or equal to 7%) are shown in Table 1. There were no adverse reactions reported in two or more patients in the placebo group (N=20).

Table 1: Adverse Reactions [Reported in at least 2 VIOKACE-treated patients (greater than or equal to 7%) and at a higher rate than placebo-treated patients.] in a Clinical Trial of Adult Patients with Exocrine Pancreatic Insufficiency Due to Chronic Pancreatitis or Pancreatectomy
Adverse Reaction | VIOKACE N = 30 (%)
Anal pruritus | 2 (7%)
Biliary tract stones | 2 (7%)

The following adverse reactions were reported in one VIOKACE-treated patient each: anemia, abdominal pain, ascites, flatulence, headache, hydocholecystis, peripheral edema, rash, renal cyst, and viral infection.

6.2. Postmarketing Experience

The following adverse reactions have been identified during post-approval use of VIOKACE or other pancreatic enzyme products. Because these reactions are reported voluntarily from a population of uncertain size, it is not always possible to reliably estimate their frequency or establish a causal relationship to drug exposure.

Eye Disorders

- blurred vision

Gastrointestinal Disorders

- fibrosing colonopathy and distal intestinal obstruction syndrome
- abdominal pain, diarrhea, flatulence, constipation, and nausea

Immune System Disorders

- anaphylaxis, asthma, hives and pruritis

Investigations

- asymptomatic elevations of liver enzymes

Musculoskeletal System

- myalgia, muscle spasm

Skin and Subcutaneous Tissue Disorders

- urticaria and rash

8. USE IN SPECIFIC POPULATIONS

8.1. Pregnancy

Risk Summary

Published data from case reports with pancrelipase use in pregnant women have not identified a drug-associated risk of major birth defects, miscarriage or other adverse maternal or fetal outcomes.

Pancrelipase is minimally absorbed systematically; therefore, maternal use is not expected to result in fetal exposure to the drug. Animal reproduction studies have not been conducted with pancrelipase.

The estimated background risk of major birth defects and miscarriage for the indicated population is unknown. All pregnancies have a background risk of birth defect, loss, or other adverse outcomes. In the U.S. general population, the estimated background risk of major birth defects and miscarriage in clinically recognized pregnancies is 2 to 4% and 15 to 20%, respectively.

8.2. Lactation

Risk Summary

There are no data on the presence of pancrelipase in either human or animal milk, the effects on the breastfed infant, or the effects on milk production. Pancrelipase is minimally absorbed systemically following oral administration, therefore maternal use is not expected to result in clinically relevant exposure of breastfed infants to the drug. The developmental and health benefits of breastfeeding should be considered along with the mother's clinical need for VIOKACE and any potential adverse effects on the breastfed child from VIOKACE or from the underlying maternal conditions.

8.4. Pediatric Use

The safety and effectiveness of VIOKACE in pediatric patients have not been established.

Use of VIOKACE in pediatric patients may increase the risk of inadequate treatment of pancreatic insufficiency and result in suboptimal weight gain, malnutrition and/or need for larger doses of pancreatic enzyme replacement due to tablet degradation in the gastric environment of the stomach.

High dosages of pancreatic enzyme products have been associated with fibrosing colonopathy and colonic strictures in pediatric patients less than 12 years of age [see Warnings and Precautions (5.1)].

8.5. Geriatric Use

Clinical studies of VIOKACE did not include sufficient numbers of patients aged 65 years and over to determine whether they respond differently from younger patients. Other reported clinical experience has not identified differences in responses between patients aged 65 years and over and younger adult patients.

10. OVERDOSAGE

Chronic high dosages of pancreatic enzyme products have been associated with fibrosing colonopathy and colonic strictures [see Warnings and Precautions (5.1)]. High dosages of pancreatic enzyme products have been associated with hyperuricosuria and hyperuricemia [see Warnings and Precautions (5.3)].

11. DESCRIPTION

Pancrelipase is a pancreatic enzyme product consisting of a mixture of enzymes including lipases, proteases, and amylases, and is an extract derived from porcine pancreatic glands.

VIOKACE (pancrelipase) tablets are for oral administration and available as follows:

- 10,440 USP units of lipase; 39,150 USP units of protease; and 39,150 USP units of amylase as a tan, round biconvex tablet and have VIO9111 engraved on one side and 9111 on the other side.
- 20,880 USP units of lipase; 78,300 USP units of protease; and 78,300 USP units of amylase as a tan, oval, biconvex tablet with V^16 engraved on one side and 9116 on the other side.

Inactive ingredients in VIOKACE include colloidal silicon dioxide, croscarmellose sodium, lactose monohydrate, microcrystalline cellulose, stearic acid and talc.

12. CLINICAL PHARMACOLOGY

12.1. Mechanism of Action

Pancreatic enzyme products contain a mixture of lipases, proteases, and amylases that catalyze the hydrolysis of fats to monoglycerides, glycerol and free fatty acids, proteins into peptides and amino acids, and starches into dextrins and short chain sugars such as maltose and maltriose in the duodenum and proximal small intestine, thereby acting like digestive enzymes physiologically secreted by the pancreas.

12.2. Pharmacodynamics

For patients consuming a high fat diet in the clinical trial, the coefficient of fat absorption (CFA) was higher in patients who received VIOKACE compared to the placebo treatment group, indicating improved fat absorption [see Clinical Studies (14)].

12.3. Pharmacokinetics

Following oral administration, the lipases, proteases, and amylases released from VIOKACE are not absorbed from the gastrointestinal tract in appreciable amounts.

Drug Interactions

The lipases, proteases, and amylases of VIOKACE are not substrates of CYP enzymes or transporters. CYP enzymes or transporters mediated drug interactions are not expected.

14. CLINICAL STUDIES

A randomized, double-blind, placebo-controlled, parallel group study was conducted in 50 adult patients, aged 24 to 70 years, with exocrine pancreatic insufficiency due to chronic pancreatitis or pancreatectomy. Eighteen patients had a history of pancreatectomy (11 were treated with VIOKACE). All patients were maintained on a controlled high fat diet of 100 grams of fat per day. After a washout period (6 to 7 days), patients were randomized to a fixed dose of VIOKACE or placebo, in combination with a proton pump inhibitor: 125,280 lipase units per meal (3 meals) and 41,760 lipase units per snack (2 snacks) (6 tablets per meal and 2 tablets per snacks). Forty-nine patients completed the double-blind treatment period (6 to 7 days); 29 patients received VIOKACE, and 20 patients received placebo. Duration of exposure to VIOKACE ranged from 6 to 7 days. The majority of the subjects were White (96%) and male (82%).

Coefficient of Fat Absorption Endpoint and Results

The coefficient of fat absorption (CFA) was determined by a 72-hour stool collection during both the washout period and end of double-blind period when both fat excretion and fat ingestion were measured. The mean change in CFA at the end of the double-blind treatment period in the VIOKACE and placebo groups is shown in Table 2.

Table 2: Change in Coefficient of Fat Absorption in Adults with Exocrine Pancreatic Insufficiency Due to Chronic Pancreatitis and Pancreatectomy - Intent to Treat Population
 | VIOKACE n = 30 | Placebo n = 20
CFA [%]
Washout Period (Mean, SD) | 48 (24) | 57 (22)
End of Double-Blind Period (Mean, SD) | 86 (9) | 58 (24)
Change in CFA [p<0.0001] [%]
Treatment Difference (95% CI) | 28 (18, 37)

Subgroup analyses of the CFA results showed that mean change in CFA with VIOKACE treatment (from the washout period to the end of the double-blind period) was greater in patients with lower washout period CFA values than in patients with higher washout period CFA values.

Only 2 of the patients with a history of total pancreatectomy were treated with VIOKACE. One of these patients had a CFA of 12% during the washout period and a CFA of 90% at the end of the double-blind period; the other patient had a CFA of 38% during the wash-out period and a CFA of 77% at the end of the double-blind period. The remaining 9 patients with a history of partial pancreatectomy treated with VIOKACE had a mean CFA of 56% during the washout period and a mean CFA of 86% at the end of the double-blind period.

16. HOW SUPPLIED/STORAGE AND HANDLING

VIOKACE (pancrelipase) tablets are supplied as follows:

Strength | Description | Supplied As | NDC Number
10,440 USP units of lipase; 39,150 USP units of protease; 39,150 USP units of amylase | tan, round, biconvex tablet with VIO9111 engraved on one side and 9111 on the other side | bottles of 100 | 73562-104-10
20,880 USP units of lipase; 78,300 USP units of protease; 78,300 USP units of amylase | tan, oval, biconvex tablet with V^16 engraved on one side and 9116 on the other side | bottles of 100 | 73562-208-10

Storage and Handling

- Store VIOKACE at room temperature 20°C to 25°C (68°F to 77°F), and protect from moisture. Brief excursions permitted up to 40°C (104°F) for 24 hours. After opening, keep the container tightly closed between uses to protect from moisture.
- Store and dispense VIOKACE in the original container.
- VIOKACE is dispensed in bottles containing a desiccant.

17. PATIENT COUNSELING INFORMATION

Advise the patient or caregiver to read the FDA-approved patient labeling (Medication Guide).

Fibrosing Colonopathy

Advise patients that if signs and symptoms of colon stricture formation occur (e.g., stomach area (abdominal) pain, bloating, trouble passing stool (constipation), nausea, vomiting, diarrhea) to immediately contact their healthcare provider [see Warnings and Precautions (5.1)].

Hyperuricemia

Advise the patient that hyperuricemia may occur in patients with gout or renal impairment and to contact the healthcare provider if they experience pain, stiffness, redness or swelling of their joints [see Warnings and Precautions (5.3)].

Hypersensitivity Reactions

Inform the patient that severe hypersensitivity reactions, including anaphylaxis asthma, hives, and pruritus, have been reported with use of pancreatic enzyme products. Seek medical attention if signs or symptoms of a hypersensitivity reaction develop [see Warnings and Precautions (5.5)].

Dosage

Advise the patient to take VIOKACE as prescribed, and to contact the healthcare provider if signs and symptoms of malabsorption persist [see Dosage and Administration (2.1)].

Administration

Instruct the patient to:

- Take VIOKACE with meals or snacks.
- Swallow tablets whole. Do not crush or chew VIOKACE tablets.
- Consume sufficient liquids (water) to ensure complete swallowing of VIOKACE tablets.

Storage

Instruct the patient or caregiver as follows:

- Keep VIOKACE in a dry place and protect from moisture and heat.
- After opening, keep the container tightly closed between uses to protect from moisture.
- Keep VIOKACE in the original bottle.
- The desiccant packet should not be eaten or thrown away.

Manufactured by:
Viokace LLC
1007 US Highway 202/206,
Bridgewater, NJ 08807, USA
US License No. 2196

Manufactured for:
Aimmune Therapeutics, Inc.
1007 US Highway 202/206,
Bridgewater, NJ 08807, USA

©2025 Nestlé. All trademarks are owned by Société des Produits Nestlé S.A., Vevey, Switzerland or used with permission.

MEDICATION GUIDE
VIOKACE ® (vye-oh-kase)
(pancrelipase)
tablets, for oral use

What is the most important information I should know about VIOKACE?
VIOKACE may increase your chance of having a rare bowel disorder called fibrosing colonopathy especially if taken at a high dose for a long time in children with cystic fibrosis. This condition is serious and may require surgery. The risk of having this condition may be reduced by following the dosing instructions that your doctor gave you.
Call your doctor right away if you have any unusual or severe:

- stomach area (abdominal) pain
- bloating
- trouble passing stool (having bowel movements)
- nausea, vomiting, or diarrhea

Take VIOKACE exactly as prescribed by your doctor. Do not take more VIOKACE than directed by your doctor.

What is VIOKACE?

- VIOKACE is a prescription medicine used with a proton pump inhibitor medicine (PPI) to treat adults who cannot digest food normally. Adults with swelling of the pancreas that lasts a long time (chronic pancreatitis), or who have had some or all of their pancreas removed (pancreatectomy) may not digest food normally because their pancreas does not make enough enzymes.
- VIOKACE contains a mixture of digestive enzymes (including lipases, proteases, and amylases) from pig pancreas.
- It is not known if VIOKACE is safe and effective in children. Use of VIOKACE in children may result in poor nutrition and slowing of growth.

Before taking VIOKACE, tell your doctor about all your medical conditions, including if you:

- are allergic to pork (pig) products.
- have a history of blockage of your intestines, or scarring or thickening of your bowel wall (fibrosing colonopathy).
- have gout, kidney disease, or a condition called high blood uric acid (hyperuricemia).
- have trouble swallowing tablets.
- are lactose intolerant.
- have any other medical condition.
- are pregnant or plan to become pregnant.
- are breastfeeding or plan to breastfeed. It is not known if VIOKACE passes into your breast milk. Talk to your doctor about the best way to feed your baby if you take VIOKACE.

Tell your doctor about all the medicines you take, including prescription and over-the-counter medicines, vitamins, and herbal supplements.
Know the medicines you take. Keep a list of them and show it to your doctor and pharmacist when you get a new medicine.

How should I take VIOKACE?

- Take VIOKACE tablets exactly as your doctor tells you. Contact your doctor if you continue to have signs and symptoms of malabsorption (not absorbing nutrients from food) such as abdominal pain, abdominal distention, bloating, fatty stools, or weight loss. Your dose may need to be changed.
- You should not switch VIOKACE with any other pancreatic enzyme product without first talking to your doctor.
- Do not take more tablets in a day than the number your doctor tells you to take (total daily dose).
- Always take VIOKACE with a meal or a snack and enough liquid (water) to swallow VIOKACE completely. If you eat a lot of meals or snacks in a day, be careful not to go over your total daily dose.
- Your doctor may change your dose based on the amount of fatty foods you eat or based on your weight.
- Your doctor should also prescribe a medicine for you called a proton pump inhibitor (PPI) to decrease stomach acid. VIOKACE should be taken with a PPI to help prevent VIOKACE from breaking down in your stomach.
- Swallow VIOKACE tablets whole. Do not crush or chew the tablets. Be careful to make sure that no VIOKACE is left in your mouth. Crushing or chewing the VIOKACE tablets may cause irritation in your mouth, or change the way VIOKACE works in your body.
- If you forget to take VIOKACE, wait until your next meal and take your usual number of tablets. Take your next dose at your usual time. Do not take two doses at one time.

What are the possible side effects of VIOKACE?
VIOKACE may cause serious side effects, including:

- See "What is the most important information I should know about VIOKACE?"
- Irritation of the inside of your mouth. This can happen if VIOKACE is not swallowed completely.
- Increase in blood uric acid levels (hyperuricemia). This may happen in people with gout, kidney problems, or those who take high doses of pancrelipase, the active ingredient in VIOKACE. Call your doctor if you have pain, stiffness, redness or swelling of your joints.
- Severe allergic reactions. Severe allergic reactions have happened in people taking pancreatic enzyme products like VIOKACE. Stop taking VIOKACE and get emergency treatment right away if you have any of these symptoms: trouble with breathing, skin rashes, swollen lips, or itching.

The most common side effects of VIOKACE include:

- You can develop stones that form in your gallbladder and the tubes that carry bile to your small intestines.
- anal itching

Other Possible Side Effects:
VIOKACE and other pancreatic enzyme products are made from the pancreas of pigs, the same pigs people eat as pork. These pigs may carry viruses. Although it has never been reported, it may be possible for a person to get a viral infection from taking pancreatic enzyme products that come from pigs.
Tell your doctor if you have any side effect that bothers you or that does not go away.
These are not all the possible side effects of VIOKACE.
Call your doctor for medical advice about side effects. You may report side effects to FDA at 1-800-FDA-1088.
You may also report side effects to Aimmune Therapeutics, Inc at 1-833-AIM2KNO (1-833-246-2566)

How should I store VIOKACE?

- Store VIOKACE at room temperature between 68°F to 77°F (20°C to 25°C). Avoid heat.
- Keep VIOKACE in a dry place and in its original container.
- After opening the bottle, keep it closed tightly between uses to protect from moisture.
- The VIOKACE bottle contains a desiccant packet to help keep your medicine dry (protect it from moisture). Do not eat or throw away the desiccant packet.

Keep VIOKACE and all medicines out of the reach of children.

General information about the safe and effective use of VIOKACE.
Medicines are sometimes prescribed for purposes other than those listed in a Medication Guide. Do not use VIOKACE for a condition for which it was not prescribed. Do not give VIOKACE to other people to take, even if they have the same symptoms you have. It may harm them.
You can ask your pharmacist or doctor for information about VIOKACE that is written for health professionals.

What are the ingredients in VIOKACE?
Active ingredients: lipase, protease and amylase
Inactive ingredients: colloidal silicon dioxide, croscarmellose sodium, lactose monohydrate, microcrystalline cellulose, stearic acid and talc.
Manufactured by:
Viokace LLC
1007 US Highway 202/206,
Bridgewater, NJ 08807, USA
US License No. 2196
Manufactured for:
Aimmune Therapeutics, Inc.
1007 US Highway 202/206,
Bridgewater, NJ 08807, USA
For more information, please call Aimmune Therapeutics, Inc at 1-833-AIM2KNO (1-833-246-2566).
All trademarks are owned by Société des Produits Nestlé S.A., Vevey, Switzerland or used with permission.
©2025 Nestlé.

This Medication Guide has been approved by the U.S. Food and Drug Administration.

Revised: 07/2025

PRINCIPAL DISPLAY PANEL - 100 Tablet Bottle Carton - 104-10

NDC# 73562-104-10

pancrelipase
Viokace®
TABLETS

Rx only

Each tablet contains:
10,440 USP Units Lipase
39,150 USP Units Amylase
39,150 USP Units Protease

VIOKACE® is dosed based
on lipase units.
Contains no preservatives.
Contains pork proteins.

VIOKACE® tablets should
be swallowed whole. Do not
crush or chew tablets.

Dispense the enclosed Medication
Guide to each patient.

Nestlé
HealthScience ®

100 TABLETS

PRINCIPAL DISPLAY PANEL - 100 Tablet Bottle Label - 104-10

NDC# 73562-104-10

pancrelipase
Viokace®
TABLETS

Rx only

Each tablet contains:
10,440 USP Units Lipase
39,150 USP Units Amylase
39,150 USP Units Protease

VIOKACE® is dosed based on
lipase units.

VIOKACE® tablets should be
swallowed whole. Do not crush
or chew tablets.
Dispense the enclosed Medication
Guide to each patient.

100 TABLETS

PRINCIPAL DISPLAY PANEL - 100 Tablet Bottle Carton - 208-10

NDC# 73562-208-10

pancrelipase
Viokace®
TABLETS

Rx only

Each tablet contains:
20,880 USP Units Lipase
78,300 USP Units Amylase
78,300 USP Units Protease

VIOKACE® is dosed based
on lipase units.
Contains no preservatives.
Contains pork proteins.

VIOKACE® tablets should
be swallowed whole. Do not
crush or chew tablets.

Dispense the enclosed Medication
Guide to each patient.

Nestlé
HealthScience ®

100 TABLETS

PRINCIPAL DISPLAY PANEL - 100 Tablet Bottle Label - 208-10

NDC# 73562-208-10

pancrelipase
Viokace®
TABLETS

Rx only

Each tablet contains:
20,880 USP Units Lipase
78,300 USP Units Amylase
78,300 USP Units Protease

VIOKACE® is dosed based on
lipase units.

VIOKACE® tablets should be
swallowed whole. Do not crush
or chew tablets.
Dispense the enclosed Medication
Guide to each patient.

100 TABLETS